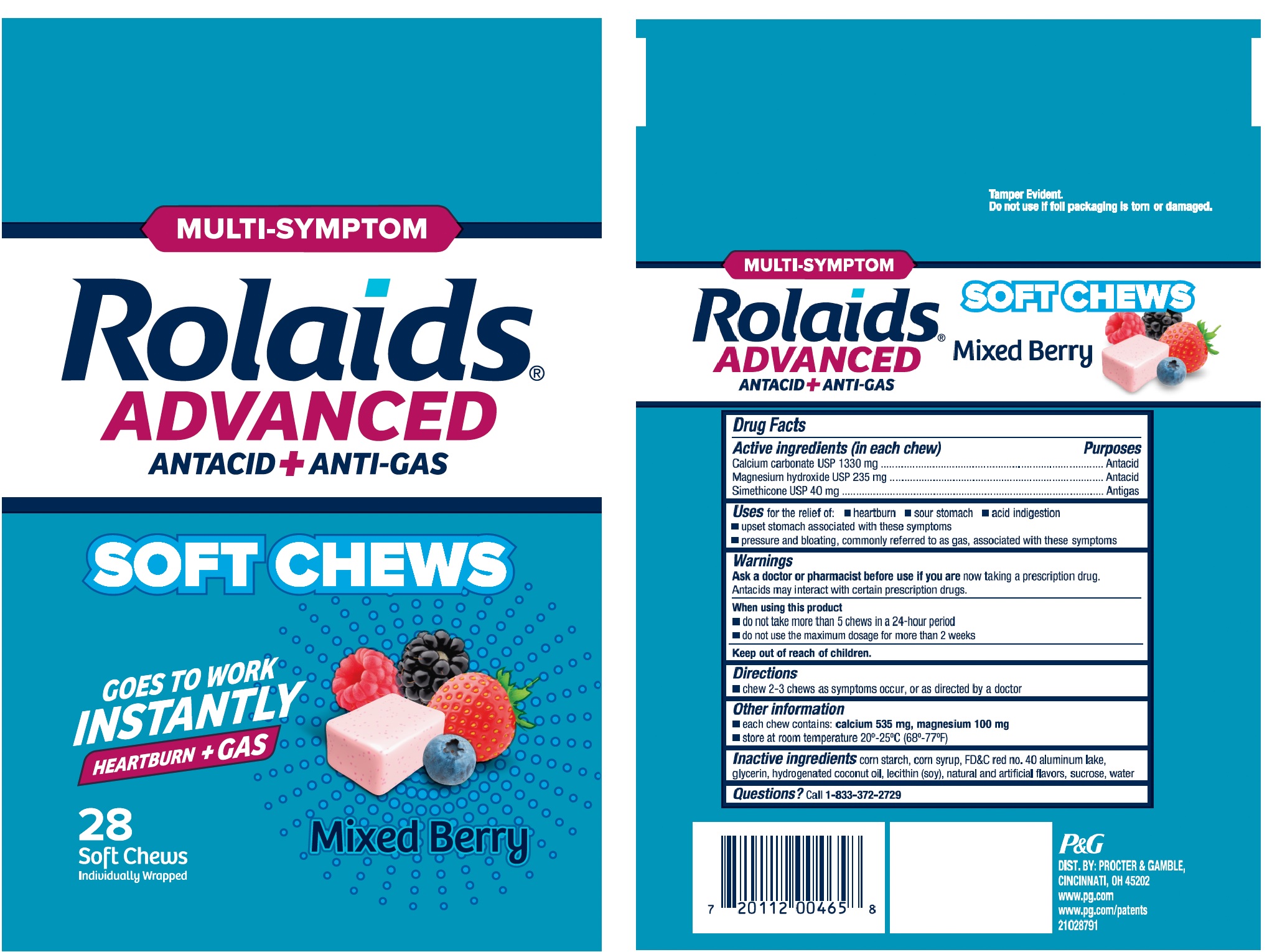 DRUG LABEL: Rolaids Advanced Antacid plus Anti-Gas

NDC: 69423-824 | Form: TABLET, CHEWABLE
Manufacturer: The Procter & Gamble Manufacturing Company
Category: otc | Type: HUMAN OTC DRUG LABEL
Date: 20251003

ACTIVE INGREDIENTS: CALCIUM CARBONATE 1330 mg/1 1; MAGNESIUM HYDROXIDE 235 mg/1 1; DIMETHICONE 40 mg/1 1
INACTIVE INGREDIENTS: ALUMINUM OXIDE; SILICON DIOXIDE; STARCH, CORN; CORN SYRUP; FD&C RED NO. 40; GLYCERIN; HYDROGENATED COCONUT OIL; LECITHIN, SOYBEAN; SUCROSE; WATER

Rolaids Advanced Antacid + Anti-Gas SOFT CHEWS

Drug Facts

Activeingredients (in eachchew)

Calcium carbonate USP 1330 mg

Magnesium hydroxide USP 235 mg

Simethicone USP 40 mg

Purposes

Antacid

Antacid

Antigas

Uses

for the relief of: ■ heartburn ■ sour stomach ■ acid indigestion ■ upset stomach associated with these symptoms ■ pressure and bloating, commonly referred to as gas, associated with these symptoms

Warnings

Ask a doctor or pharmacist before use if

youare now taking a prescription drug. Antacids may interact with certain prescription drugs.

When using this product

■ do not take more than 5 chews in a 24-hour period

■ do not use the maximum dosage for more than 2 weeks

Directions

■ chew 2-3 chews as symptoms occur, or as directed by a doctor

Other information

■ each chew contains: calcium 535 mg, magnesium 100 mg

■ store at room temperature 20°– 25°C (68°-77°F)

Inactive ingredients

corn starch, corn syrup, FD&C red no. 40 aluminum lake, glycerin, hydrogenated coconut oil, lecithin (soy), natural and artificial flavors, sucrose, water

Questions?

Call
1-833-372-2729

Tamper Evident. Do not use if foil packaging is torn or damaged.

DIST. BY PROCTER & GAMBLE,

CINCINNATI, OH 45202

PRINCIPAL DISPLAY PANEL

MULTI-SYMPTOM
Rolaids ® ADVANCED ANTACID + ANTI-GAS
SOFT CHEWS
GOES TO WORK INSTANTLY
HEARTBURN + GAS
28 Soft chews
Individually Wrapped
Mixed Berry